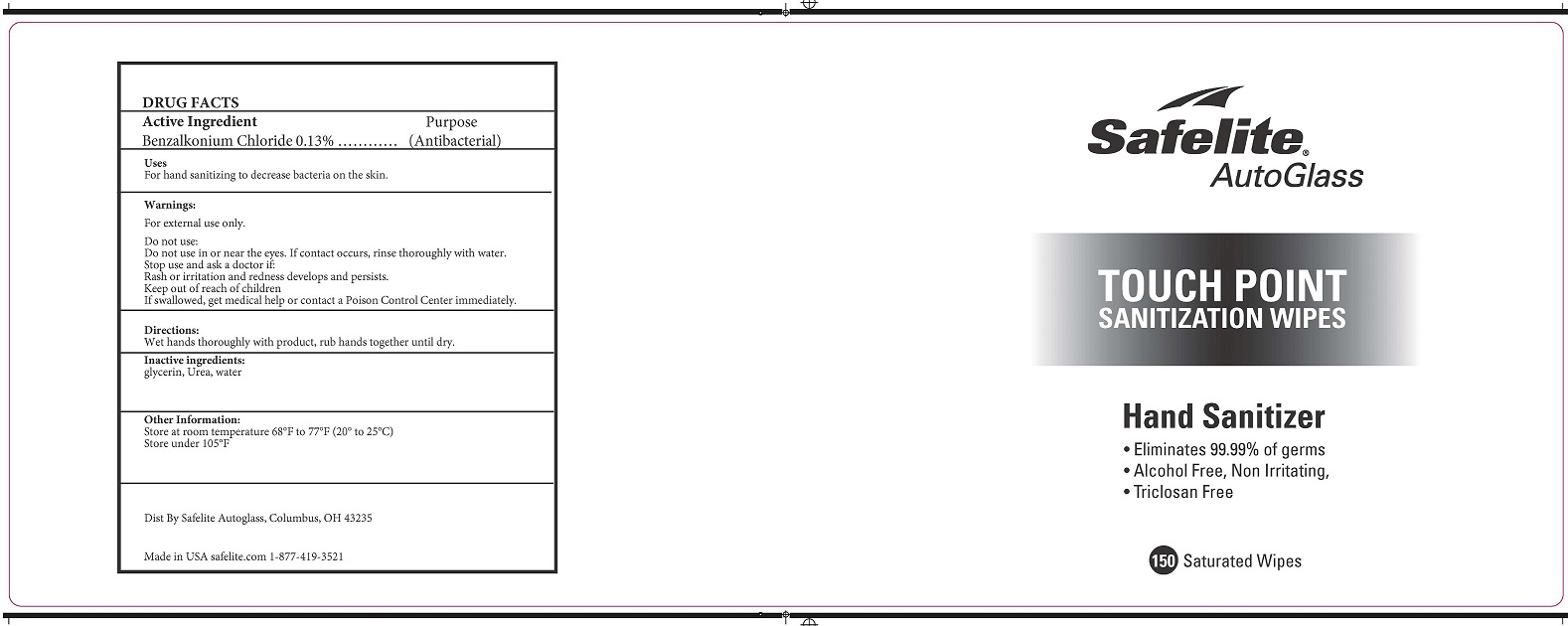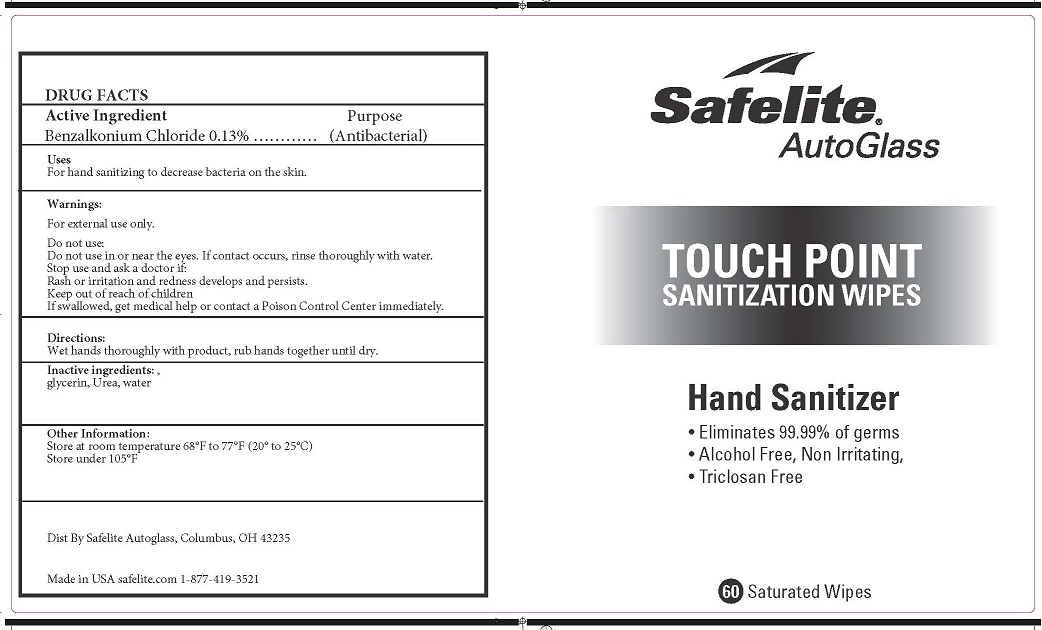 DRUG LABEL: Safelite AutoGlass Touch Point Sanitization Wipes
NDC: 52261-7400 | Form: SWAB
Manufacturer: Cosco International, Inc.
Category: otc | Type: HUMAN OTC DRUG LABEL
Date: 20200616

ACTIVE INGREDIENTS: BENZALKONIUM CHLORIDE 0.13 1/1 1
INACTIVE INGREDIENTS: GLYCERIN; UREA; WATER

Active Ingredient(s)

Benzalkonium Chloride 0.13% ...... Purpose: Antiseptic

Purpose

Antibacterial hand wipes

Use

For hand sanitizing to decrease bacteria on the skin.

Warnings

For external use only.

Do not use in or near the eyes.

WHEN USING

If contact occurs, rinse throughly with water.

Stop use and ask a doctor if rash or irritation develops or persists.

Keep out of reach of children.

If swallowed, get medical help or contact a Poison Control Center right away.

Directions

Wet hands thoroughly with product, rub hands together until dry.

Other information

- Store at room temperature 68°F to 77°F (20° to 25°C)
- Store under 105°F

Inactive ingredients

Glycerin, Urea, Water